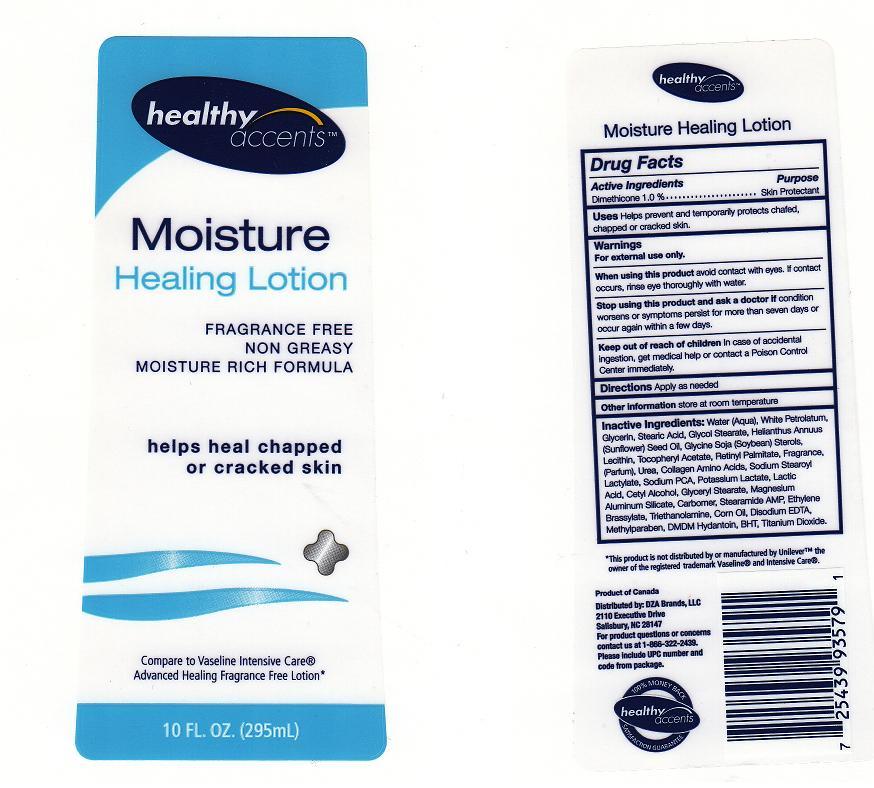 DRUG LABEL: Healthy Accents
NDC: 55316-315 | Form: LOTION
Manufacturer: DZA Brands LLC
Category: otc | Type: HUMAN OTC DRUG LABEL
Date: 20100625

ACTIVE INGREDIENTS: DIMETHICONE 1 mL/100 mL
INACTIVE INGREDIENTS: WATER; PETROLATUM; STEARIC ACID; GLYCOL STEARATE; SUNFLOWER OIL; SOY STEROL; LECITHIN, SOYBEAN; .ALPHA.-TOCOPHEROL ACETATE, D-; VITAMIN A PALMITATE; UREA; SODIUM ISOSTEAROYL LACTYLATE; SODIUM PYRROLIDONE CARBOXYLATE; POTASSIUM LACTATE; LACTIC ACID; CETYL ALCOHOL; GLYCERYL MONOSTEARATE; MAGNESIUM ALUMINUM SILICATE; CARBOMER 934; STEARAMIDOETHYL DIETHYLAMINE; ETHYLENE BRASSYLATE; TROLAMINE; CORN OIL; EDETATE DISODIUM; METHYLPARABEN; DMDM HYDANTOIN; BUTYLATED HYDROXYTOLUENE; TITANIUM DIOXIDE

BACK LABEL - DRUG FACTS BOX

ACTIVE INGREDIENT

DIMETHICONE 1.0%

WARNING

FOR EXTERNAL USE ONLY.

When using this product

AVOID CONTACT WITH EYES, IF CONTACT OCCURS, RINSE EYE THROUGHLY WITH WATER.

STOP USING THIS PRODUCT AND ASK A DOCTOR IF

CONDITION WORSENS OR SYMPTOMS PERSIST FOR MORE THAN SEVEN DAYS OR OCCUR AGAIN WITHIN A FEW DAYS.

KEEP OUT OF REACH OF CHILDREN

IN CASE OF ACCIDENTAL INGESTION, GET MEDICAL HELP OR CONTACT A POISON CONTROL CENTER IMMEDIATELY.

Purpose

Skin Protectant

Uses

HELPS PREVENT AND TEMPORARILY PROTECTS CHAFED, CHAPPED OR CRACKED SKIN

Directions

APPLY AS NEEDED.

Inactive Ingredients

Water, White Petrolatum, Glycerin, Stearic Acid, Glycol Stearate, Helianthus Annuus (Sunflower) Seed Oil, Glycine Soja (Soybean) Sterols, Lecithin, Tocopheryl Acetate, Retinyl Palmitate, Fragrance, Urea, Collagen Amino Acids, Sodium Stearoyl Lactylate, Sodium PCA, Potassium Lactate, Lactic Acid, Cetyl Alcohol, Glyceryl Stearate, Magnesium Aluminum Silicate, Carbomer, Stearamide AMP, Ethylene Brassylate, Triethanolamine, Corn Oil, Disodium EDTA, Methylparaben, DMDM Hydantoin, BHT, Titanium Dioxide

Package Front and Back Labels

10 OZ Front and Back Labels: hac10.jpg